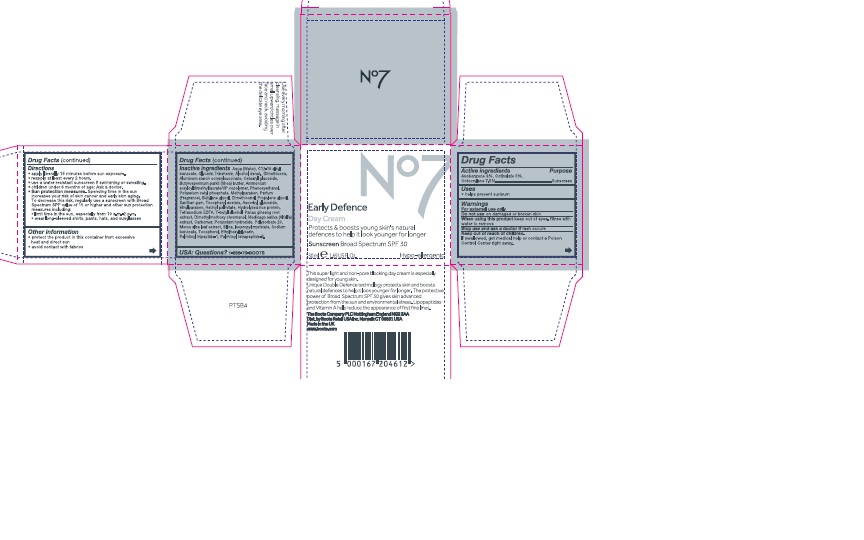 DRUG LABEL: No7 Early Defence Day Cream
NDC: 11489-097 | Form: CREAM
Manufacturer: BCM Ltd
Category: otc | Type: HUMAN OTC DRUG LABEL
Date: 20160201

ACTIVE INGREDIENTS: AVOBENZONE 1.5 g/1 g; OCTOCRYLENE 3.75 g/1 g; OCTISALATE 2.5 g/1 g
INACTIVE INGREDIENTS: WATER; GLYCERIN; ALUMINUM STARCH OCTENYLSUCCINATE; CETEARYL GLUCOSIDE; DIMETHICONE; TRIBEHENIN; AMMONIUM ACRYLOYLDIMETHYLTAURATE/VP COPOLYMER; PHENOXYETHANOL; SHEA BUTTER; POTASSIUM CETYL PHOSPHATE; BUTYLENE GLYCOL; DIMETHICONOL (100000 CST); PROPYLENE GLYCOL; METHYLPARABEN; ETHYLPARABEN; XANTHAN GUM; PANAX GINSENG ROOT OIL; VITAMIN A PALMITATE; ASCORBYL GLUCOSIDE; EDETATE SODIUM; TERT-BUTYL ALCOHOL; DIMETHYLMETHOXY CHROMANOL; POLYSORBATE 20; MEDICAGO SATIVA LEAF; POTASSIUM HYDROXIDE; CARBOMER 940; MORUS ALBA LEAF; ISOPROPYL MYRISTATE; SODIUM BENZOATE; ETHYLHEXYLGLYCERIN; TOCOPHEROL; PALMITOYL TRIPEPTIDE-1; PALMITOYL TETRAPEPTIDE-7

No7 Early Defence Day Cream Sunscreen Broad Spectrum SPF 30

Carton Active Ingredients Section

Active ingredients

Avobenzone 3%

Octisalate 5%

Octocrylene 7.5%

Uses

Uses - helps prevent sunburn

Warnings

For external use only

Do not use on damaged or broken skin

When using this product keep out of eyes. Rinse with water to remove.

Ask a doctor

Stop use and ask a doctor if rash occurs

Keep out of reach of children

If swallowed, get medical help or contact a Poison Control Center right away

Directions

Apply liberally 15 minutes before sun exposure

reapply at least every 2 hours

use a water resistant sunscreen if swimming or sweating

children under 6 months of age: Ask a doctor

Sun Protection Measures. Spending time in the sun increases your risk of skin cancer and early skin aging.

To decrease this risk, regularly use a sunscreen with a Broad Spectrum SPF value of 15 or higher and other sun protection measures including:

Limit time in the sun, especially from 10 a.m - 2 p.m.

wear long-sleeved shirts,pants,hats and sunglasses.

Storage

Other information

Protect the product in this container from excessive heat and direct sun

Avoid contact with fabrics

Inactive ingredients

Aqua(Water), Glycerin, C12-15 alkyl benzoate,Tribehenin, Alcohol denat, Dimethicone, Aluminum starch octenylsuccinate, Cetearyl glucoside, Butyrospermum parkii(Shea)butter, Ammonium acryloydimethyltaurate/VP copolymer, Phenoxyethanol, Potassium cetyl phosphate, Methylparaben, Parfum(Fragrance), Butylene glycol, Dimethiconol, Propylene glycol, Xanthan gum, Tocopheryl acetate, Ascorbyl glucoside, Ethylparaben, Retinyl palmitate, Hydrolyzed rice protein, Tetrasodium EDTA, T-butyl alcohol, Panax ginseng root extract, Dimethylmethoxy chromanol, Medicago sativa(Alfalfa) extract, Carbomer, Potassium hydroxide, Polysorbate 20, Morus alba leaf extract, Silica, Isopropyl myristate, Sodium benzoate, Tocopherol, Ethylhexylglycerin, Palmitoyl tripeptide-1, Palmitoyl tetrapeptide-7

Description

Protects and boosts young skin's natural defences to help it look younger for longer.

This super light and non-pore blocking day cream is especially designed for young skin.

Unique Double Defence technology protects skin and boosts natural defences to help it look younger for longer. The protective power of Broad Spectrum SPF30 gives skin advanced protection from the sun and environmental stress. Lipopeptides and Vitamin A help reduce the appearance of first fine lines.

Use every morning after cleansing, massage in small upward circles over face and neck,avoiding the delicate eye area.

PATIENT COUNSELING INFORMATION

Made in the UK

The Boots Company PLC Nottingham England NG2 3AA

Dist. by Boots Retail USA Inc. Norwalk CT 06851 USA

www.boots.com